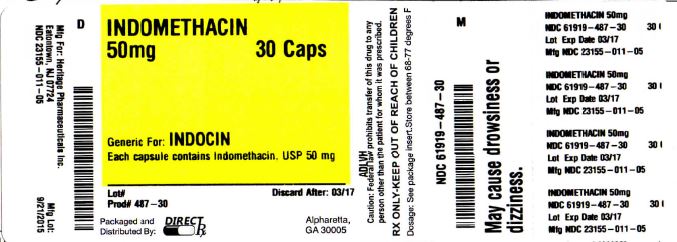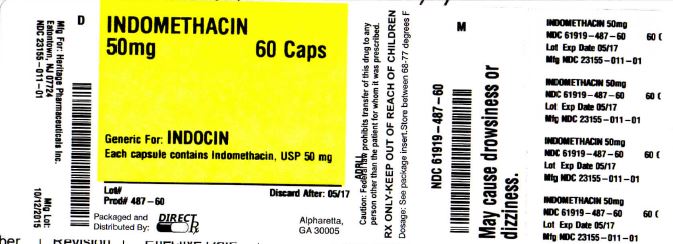 DRUG LABEL: INDOMETHACIN
NDC: 61919-487 | Form: CAPSULE
Manufacturer: DirectRX
Category: prescription | Type: HUMAN PRESCRIPTION DRUG LABEL
Date: 20151021

ACTIVE INGREDIENTS: INDOMETHACIN 50 mg/1 1
INACTIVE INGREDIENTS: D&C RED NO. 28; FD&C BLUE NO. 1; FD&C RED NO. 3; GELATIN; LACTOSE MONOHYDRATE; MAGNESIUM STEARATE; POVIDONE; SILICON DIOXIDE; SODIUM LAURYL SULFATE; STARCH, CORN; TITANIUM DIOXIDE

INDOMETHACIN

BOXED WARNING SECTION

- BOXED WARNINGS
  Cardiovascular Risk
  • NSAIDs may cause an increased risk of serious cardiovascular thrombotic events, myocardial infarction, and stroke, which can be fatal. This risk may increase with duration of use. Patients with cardiovascular disease or risk factors for cardiovascular disease may be at a greater risk. (See WARNINGS.)
  • Indomethacin is contraindicated for the treatment of peri-operative pain in the setting of coronary artery bypass graft (CABG) surgery (see WARNINGS).
  Gastrointestinal Risk
  • NSAIDs cause an increased risk of serious gastrointestinal adverse events including bleeding, ulceration, and perforation of the stomach or intestines, which can be fatal. These events can occur at any time during use and without warning symptoms. Elderly patients are at greater risk for serious gastrointestinal events. (See WARNINGS.)

DESCRIPTION SECTION

Indomethacin Capsules, USP for oral administration contain either 25 mg or 50 mg of indomethacin and the following inactive ingredients: D & C Red #28, FD&C Blue #1, FD&C Red #3, gelatin, lactose monohydrate, magnesium stearate, povidone, pregelatinized starch, silicon dioxide, sodium lauryl sulfate, starch and titanium dioxide. Indomethacin is a non-steroidal anti-inflammatory indole derivative designated chemically as 1-(4-chlorobenzoyl)-5-methoxy-2-methyl-1H-indole-3-acetic acid. Indomethacin is practically insoluble in water and sparingly soluble in alcohol. It has a pKa of 4.5 and is stable in neutral or slightly acidic media and decomposes in strong alkali.

CLINICAL PHARMACOLOGY SECTION

- Indomethacin is a non-steroidal anti-inflammatory drug (NSAID) that exhibits antipyretic and analgesic properties. Its mode of action, like that of other anti-inflammatory drugs, is not known. However, its therapeutic action is not due to pituitary-adrenal stimulation.
  Indomethacin is a potent inhibitor of prostaglandin synthesis in vitro. Concentrations are reached during therapy which have been demonstrated to have an effect in vivo as well. Prostaglandins sensitize afferent nerves and potentiate the action of bradykinin in inducing pain in animal models. Moreover, prostaglandins are known to be among the mediators of inflammation. Since indomethacin is an inhibitor of prostaglandin synthesis, its mode of action may be due to a decrease of prostaglandins in peripheral tissues.
  Indomethacin has been shown to be an effective anti-inflammatory agent, appropriate for long-term use in rheumatoid arthritis, ankylosing spondylitis, and osteoarthritis.
  Indomethacin affords relief of symptoms; it does not alter the progressive course of the underlying disease.
  Indomethacin suppresses inflammation in rheumatoid arthritis as demonstrated by relief of pain, and reduction of fever, swelling and tenderness. Improvement in patients treated with indomethacin for rheumatoid arthritis has been demonstrated by a reduction in joint swelling, average number of joints involved, and morning stiffness; by increased mobility as demonstrated by a decrease in walking time; and by improved functional capability as demonstrated by an increase in grip strength. Indomethacin may enable the reduction of steroid dosage in patients receiving steroids for the more severe forms of rheumatoid arthritis. In such instances the steroid dosage should be reduced slowly and the patients followed very closely for any possible adverse effects.
  Indomethacin has been reported to diminish basal and CO2 stimulated cerebral blood flow in healthy volunteers following acute oral and intravenous administration. In one study after one week of treatment with orally administered indomethacin, this effect on basal cerebral blood flow had disappeared. The clinical significance of this effect has not been established.
  Indomethacin capsules have been found effective in relieving the pain, reducing the fever, swelling, redness, and tenderness of acute gouty arthritis - see INDICATIONS AND USAGE.
  Following single oral doses of indomethacin capsules 25 mg or 50 mg, indomethacin is readily absorbed, attaining peak plasma concentrations of about 1 and 2 mcg/mL, respectively, at about 2 hours. Orally administered indomethacin capsules are virtually 100% bioavailable, with 90% of the dose absorbed within 4 hours. A single 50 mg dose of indomethacin oral suspension was found to be bioequivalent to a 50 mg indomethacin capsule when each was administered with food.
  Indomethacin is eliminated via renal excretion, metabolism, and biliary excretion. Indomethacin undergoes appreciable enterohepatic circulation. The mean half-life of indomethacin is estimated to be about 4.5 hours. With a typical therapeutic regimen of 25 or 50 mg t.i.d., the steady-state plasma concentrations of indomethacin are an average 1.4 times those following the first dose.
  Indomethacin exists in the plasma as the parent drug and its desmethyl, desbenzoyl, and desmethyl-desbenzoyl metabolites, all in the unconjugated form. About 60% of an oral dosage is recovered in urine as drug and metabolites (26% as indomethacin and its glucuronide), and 33% is recovered in feces (1.5% as indomethacin).
  About 99% of indomethacin is bound to protein in plasma over the expected range of therapeutic plasma concentrations. Indomethacin has been found to cross the blood-brain barrier and the placenta.

INDICATIONS & USAGE SECTION

- Carefully consider the potential benefits and risks of indomethacin and other treatment options before deciding to use indomethacin. Use the lowest effective dose for the shortest duration consistent with individual patient treatment goals (see WARNINGS).
  Indomethacin has been found effective in active stages of the following:
  1. Moderate to severe rheumatoid arthritis including acute flares of chronic disease.
  2. Moderate to severe ankylosing spondylitis.
  3. Moderate to severe osteoarthritis.
  4. Acute painful shoulder (bursitis and/or tendinitis).
  5. Acute gouty arthritis.

CONTRAINDICATIONS SECTION

- Indomethacin is contraindicated in patients with known hypersensitivity to indomethacin or the excipients (see DESCRIPTION).
  Indomethacin should not be given to patients who have experienced asthma, urticaria, or allergic-type reactions after taking aspirin or other NSAIDs. Severe, rarely fatal, anaphylactic/anaphylactoid reactions to NSAIDs have been reported in such patients (see WARNINGS - Anaphylactic/Anaphylactoid Reactions, and PRECAUTIONS - Preexisting Asthma).
  Indomethacin is contraindicated for the treatment of peri-operative pain in the setting of coronary artery bypass graft (CABG) surgery (see WARNINGS).

WARNINGS SECTION

- CARDIOVASCULAR EFFECTS
  Cardiovascular Thrombotic Events
  Clinical trials of several COX-2 selective and nonselective NSAIDs of up to three years duration have shown an increased risk of serious cardiovascular (CV) thrombotic events, myocardial infarction, and stroke, which can be fatal. All NSAIDs, both COX-2 selective and nonselective, may have a similar risk. Patients with known CV disease or risk factors for CV disease may be at greater risk. To minimize the potential risk for an adverse CV event in patients treated with an NSAID, the lowest effective dose should be used for the shortest duration possible. Physicians and patients should remain alert for the development of such events, even in the absence of previous CV symptoms. Patients should be informed about the signs and/or symptoms of serious CV events and the steps to take if they occur.
  There is no consistent evidence that concurrent use of aspirin mitigates the increased risk of serious CV thrombotic events associated with NSAID use. The concurrent use of aspirin and an NSAID does increase the risk of serious GI events (see GI WARNINGS).
  Two large, controlled, clinical trials of a COX-2 selective NSAID for the treatment of pain in the first 10-14 days following CABG surgery found an increased incidence of myocardial infarction and stroke (see CONTRAINDICATIONS).
  Hypertension
  NSAIDs, including indomethacin, can lead to onset of new hypertension or worsening of pre-existing hypertension, either of which may contribute to the increased incidence of CV events. Patients taking thiazides or loop diuretics may have impaired response to these therapies when taking NSAIDs. NSAIDs, including indomethacin, should be used with caution in patients with hypertension. Blood pressure (BP) should be monitored closely during the initiation of NSAID treatment and throughout the course of therapy.
  Congestive Heart Failure and Edema
  Fluid retention and edema have been observed in some patients taking NSAIDs. Indomethacin should be used with caution in patients with fluid retention or heart failure.
  In a study of patients with severe heart failure and hyponatremia, indomethacin was associated with significant deterioration of circulatory hemodynamics, presumably due to inhibition of prostaglandin dependent compensatory mechanisms.
  Gastrointestinal Effects - Risk of Ulceration, Bleeding, and Perforation
  NSAIDs, including indomethacin, can cause serious gastrointestinal (GI) adverse events including inflammation, bleeding, ulceration, and perforation of the esophagus, stomach, small intestine, or large intestine, which can be fatal. These serious adverse events can occur at any time, with or without warning symptoms, in patients treated with NSAIDs. Only one in five patients, who develop a serious upper GI adverse event on NSAID therapy is symptomatic. Upper GI ulcers, gross bleeding, or perforation caused by NSAIDs occur in approximately 1% of patients treated for 3 - 6 months, and in about 2 – 4% of patients treated for one year. These trends continue with longer duration of use, increasing the likelihood of developing a serious GI event at some time during the course of therapy. However, even short-term therapy is not without risk.
  Rarely, in patients taking Indomethacin, intestinal ulceration has been associated with stenosis and obstruction. Gastrointestinal bleeding without obvious ulcer formation and perforation of pre-existing sigmoid lesions (diverticulum, carcinoma, etc.) have occurred. Increased abdominal pain in ulcerative colitis patients or the development of ulcerative colitis and regional ileitis have been reported to occur rarely.
  NSAIDs should be prescribed with extreme caution in those with prior history of ulcer disease or gastrointestinal bleeding. Patients with a prior history of peptic ulcer disease and/or gastrointestinal bleeding who use NSAIDs have a greater than 10-fold increased risk for developing a GI bleed compared to patients with neither of these risk factors. Other factors that increase the risk for GI bleeding in patients treated with NSAIDs include concomitant use of oral corticosteroids or anticoagulants, longer duration of NSAID therapy, smoking, use of alcohol, older age, and poor general health status. Most spontaneous reports of fatal GI events are in elderly or debilitated patients and therefore, special care should be taken in treating this population.
  To minimize the potential risk for an adverse GI event in patients treated with an NSAID, the lowest effective dose should be used for the shortest possible duration. Patients and physicians should remain alert for signs and symptoms of GI ulceration and bleeding during NSAID therapy and promptly initiate additional evaluation and treatment if a serious GI adverse event is suspected. This should include discontinuation of the NSAID until a serious GI adverse event is ruled out. For high risk patients, alternate therapies that do not involve NSAIDs should be considered.
  Renal Effects
  Long-term administration of NSAIDs has resulted in renal papillary necrosis and other renal injury. Renal toxicity has also been seen in patients in whom renal prostaglandins have a compensatory role in the maintenance of renal perfusion. In these patients, administration of a nonsteroidal anti-inflammatory drug may cause a dose-dependent reduction in prostaglandin formation and, secondarily, in renal blood flow, which may precipitate over renal decompensation. Patients at greatest risk of this reaction are those with impaired renal function, heart failure, liver dysfunction, those taking diuretics and ACE inhibitors, patients with volume depletion, and the elderly. Discontinuation of NSAID therapy is usually followed by recovery to the pretreatment state.
  Increases in serum potassium concentration, including hyperkalemia, have been reported with use of indomethacin, even in some patients without renal impairment. In patients with normal renal function, these effects have been attributed to a hyporeninemic-hypoaldosteronism state (see PRECAUTIONS, Drug Interactions).
  Advanced Renal Disease
  No information is available from controlled clinical studies regarding the use of indomethacin in patients with advanced renal disease. Therefore, treatment with indomethacin is not recommended in these patients with advanced renal disease. If indomethacin therapy must be initiated, close monitoring of the patient’s renal function is advisable.
  Anaphylactic/Anaphylactoid Reactions
  As with other NSAIDs, anaphylactic/anaphylactoid reactions may occur in patients without known prior exposure to indomethacin. Indomethacin should not be given to patients with the aspirin triad. This symptom complex typically occurs in asthmatic patients who experience rhinitis with or without nasal polyps, or who exhibit severe, potentially fatal bronchospasm after taking aspirin or other NSAIDs (see CONTRAINDICATIONS and PRECAUTIONS - Preexisting Asthma). Emergency help should be sought in cases where an anaphylactic/anaphylactoid reaction occurs.
  Skin Reactions
  NSAIDs, including indomethacin, can cause serious skin adverse events such as exfoliative dermatitis, Stevens Johnson Syndrome (SJS), and toxic epidermal necrolysis (TEN), which can be fatal. These serious events may occur without warning. Patients should be informed about the signs and symptoms of serious skin manifestations and use of the drug should be discontinued at the first appearance of skin rash or any other sign of hypersensitivity.
  Pregnancy
  In late pregnancy, as with other NSAIDs, Indomethacin should be avoided because it may cause premature closure of the ductus arteriosus.
  Ocular Effects:
  Corneal deposits and retinal disturbances, including those of the macula, have been observed in some patients who had received prolonged therapy with Indomethacin. The prescribing physician should be alert to the possible association between the changes noted and Indomethacin. It is advisable to discontinue therapy if such changes are observed. Blurred vision may be a significant symptom and warrants a thorough ophthalmological examination. Since these changes may be asymptomatic, ophthalmologic examination at periodic intervals is desirable in patients where therapy is prolonged.
  Central Nervous System Effects:
  Indomethacin may aggravate depression or other psychiatric disturbances, epilepsy, and parkinsonism, and should be used with considerable caution in patients with these conditions. If severe CNS adverse reactions develop, Indomethacin should be discontinued.
  Indomethacin may cause drowsiness; therefore, patients should be cautioned about engaging in activities requiring mental alertness and motor coordination, such as driving a car. Indomethacin may also cause headache. Headache which persists despite dosage reduction requires cessation of therapy with indomethacin.

PRECAUTIONS SECTION

- General
  Indomethacin cannot be expected to substitute for corticosteroids or to treat corticosteroid insufficiency. Abrupt discontinuation of corticosteroids may lead to disease exacerbation. Patients on prolonged corticosteroid therapy should have their therapy tapered slowly if a decision is made to discontinue corticosteroids.
  The pharmacological activity of Indomethacin in reducing fever and inflammation may diminish the utility of these diagnostic signs in detecting complications of presumed noninfectious, painful conditions.
  Hepatic Effects
  Borderline elevations of one or more liver tests may occur in up to 15% of patients taking NSAIDs including indomethacin. These laboratory abnormalities may progress, may remain unchanged, or may be transient with continuing therapy. Notable elevations of ALT or AST (approximately three or more times the upper limit of normal) have been reported in approximately 1% of patients in clinical trials with NSAIDs. In addition, rare cases of severe hepatic reactions, including jaundice and fatal fulminant hepatitis, liver necrosis and hepatic failure, some of them with fatal outcomes have been reported.
  A patient with symptoms and/or signs suggesting liver dysfunction, or in whom an abnormal liver test has occurred, should be evaluated for evidence of the development of a more severe hepatic reaction while on therapy with indomethacin. If clinical signs and symptoms consistent with liver disease develop, or if systemic manifestations occur (e.g., eosinophilia, rash, etc.), indomethacin should be discontinued.
  Hematological Effects
  Anemia is sometimes seen in patients receiving NSAIDs, including indomethacin. This may be due to fluid retention, occult or gross GI blood loss, or an incompletely described effect upon erythropoiesis. Patients on long-term treatment with NSAIDs, including indomethacin, should have their hemoglobin or hematocrit checked if they exhibit any signs or symptoms of anemia.
  NSAIDs inhibit platelet aggregation and have been shown to prolong bleeding time in some patients. Unlike aspirin, their effect on platelet function is quantitatively less, of shorter duration, and reversible. Patients receiving indomethacin who may be adversely affected by alterations in platelet function, such as those with coagulation disorders or patients receiving anticoagulants, should be carefully monitored.
  Preexisting Asthma
  Patients with asthma may have aspirin-sensitive asthma. The use of aspirin in patients with aspirin-sensitive asthma has been associated with severe bronchospasm which can be fatal. Since cross reactivity, including bronchospasm, between aspirin and other nonsteroidal anti-inflammatory drugs has been reported in such aspirin-sensitive patients, indomethacin should not be administered to patients with this form of aspirin sensitivity and should be used with caution in patients with preexisting asthma.
  Information for Patients
  Patients should be informed of the following information before initiating therapy with an NSAID and periodically during the course of ongoing therapy. Patients should also be encouraged to read the NSAID Medication Guide that accompanies each prescription dispensed.
  1. Indomethacin, like other NSAIDs, may cause serious CV side effects, such as MI or stroke, which may result in hospitalization and even death. Although serious CV events can occur without warning symptoms, patients should be alert for the signs and symptoms of chest pain, shortness of breath, weakness, slurring of speech, and should ask for medical advice when observing any indicative sign or symptoms. Patients should be apprised of the importance of this follow-up (see WARNINGS, Cardiovascular Effects).
  2. Indomethacin, like other NSAIDs, can cause GI discomfort and, rarely, serious GI side effects, such as ulcers and bleeding, which may result in hospitalization and even death. Although serious GI tract ulcerations and bleeding can occur without warning symptoms, patients should be alert for the signs and symptoms of ulcerations and bleeding, and should ask for medical advice when observing any indicative sign or symptoms including epigastric pain, dyspepsia, melena, and hematemesis. Patients should be apprised of the importance of this follow-up (see WARNINGS, Gastrointestinal Effects - Risk of Ulceration, Bleeding, and Perforation).
  3. Indomethacin, like other NSAIDs, can cause serious skin side effects such as exfoliative dermatitis, SJS, and TEN, which may result in hospitalizations and even death. Although serious skin reactions may occur without warning, patients should be alert for the signs and symptoms of skin rash and blisters, fever, or other signs of hypersensitivity such as itching, and should ask for medical advice when observing any indicative signs or symptoms. Patients should be advised to stop the drug immediately if they develop any type of rash and contact their physicians as soon as possible.
  4. Patients should promptly report signs or symptoms of unexplained weight gain or edema to their physicians.
  5. Patients should be informed of the warning signs and symptoms of hepatotoxicity (e.g., nausea, fatigue, lethargy, pruritus, jaundice, right upper quadrant tenderness, and “flu-like” symptoms). If these occur, patients should be instructed to stop therapy and seek immediate medical therapy.
  6. Patients should be informed of the signs of an anaphylactic/anaphylactoid reaction (e.g. difficulty breathing, swelling of the face or throat). If these occur, patients should be instructed to seek immediate emergency help (see WARNINGS).
  7. In late pregnancy, as with other NSAIDs, indomethacin should be avoided because it may cause premature closure of the ductus arteriosus.
  Laboratory Tests
  Because serious GI tract ulcerations and bleeding can occur without warning symptoms, physicians should monitor for signs or symptoms of GI bleeding. Patients on long-term treatment with NSAIDs should have their CBC and a chemistry profile checked periodically. If clinical signs and symptoms consistent with liver or renal disease develop, systemic manifestations occur (e.g., eosinophilia, rash, etc.) or if abnormal liver tests persist or worsen, indomethacin should be discontinued.
  Drug Interactions
  ACE-Inhibitors and Angiotensin II Antagonists
  Reports suggest that NSAIDs may diminish the antihypertensive effect of ACE-inhibitors and angiotensin II antagonists. Indomethacin can reduce the antihypertensive effects of captopril and losartan. These interactions should be given consideration in patients taking NSAIDs concomitantly with ACE-inhibitors or angiotensin II antagonists. In some patients with compromised renal function, the co-administration of an NSAID and an ACE-inhibitor or an angiotensin II antagonist may result in further deterioration of renal function, including possible acute renal failure, which is usually reversible.
  Aspirin
  When indomethacin is administered with aspirin, its protein binding is reduced, although the clearance of free indomethacin is not altered. The clinical significance of this interaction is not known.
  The use of indomethacin in conjunction with aspirin or other salicylates is not recommended. Controlled clinical studies have shown that the combined use of indomethacin and aspirin does not produce any greater therapeutic effect than the use of indomethacin alone. In a clinical study of the combined use of indomethacin and aspirin, the incidence of gastrointestinal side effects was significantly increased with combined therapy.
  In a study in normal volunteers, it was found that chronic concurrent administration of 3.6 g of aspirin per day decreases indomethacin blood levels approximately 20%.
  Beta-adrenoceptor blocking agents
  Blunting of the antihypertensive effect of beta adrenoceptor blocking agents by non-steroidal anti-inflammatory drugs including indomethacin has been reported. Therefore, when using these blocking agents to treat hypertension, patients should be observed carefully in order to confirm that the desired therapeutic effect has been obtained.
  Cyclosporine
  Administration of non-steroidal anti-inflammatory drugs concomitantly with cyclosporine has been associated with an increase in cyclosporine-induced toxicity, possibly due to decreased synthesis of renal prostacyclin. NSAIDs should be used with caution in patients taking cyclosporine, and renal function should be carefully monitored.
  Diflunisal
  In normal volunteers receiving indomethacin, the administration of diflunisal decreased the renal clearance and significantly increased the plasma levels of indomethacin. In some patients, combined use of indomethacin and diflunisal has been associated with fatal gastrointestinal hemorrhage. Therefore, diflunisal and indomethacin should not be used concomitantly.
  Digoxin
  Indomethacin given concomitantly with digoxin has been reported to increase the serum concentration and prolong the half life of digoxin. Therefore, when indomethacin and digoxin are used concomitantly, serum digoxin levels should be closely monitored.
  Diuretics
  In some patients, the administration of indomethacin can reduce the diuretic, natriuretic, and antihypertensive effects of loop, potassium-sparing, and thiazide diuretics. This response has been attributed to inhibition of renal prostaglandin synthesis.
  Indomethacin reduces basal plasma renin activity (PRA), as well as those elevations of PRA induced by furosemide administration, or salt or volume depletion. These facts should be considered when evaluating plasma renin activity in hypertensive patients.
  It has been reported that the addition of triamterene to a maintenance schedule of indomethacin resulted in reversible acute renal failure in two of four healthy volunteers. Indomethacin and triamterene should not be administered together.
  Indomethacin and potassium-sparing diuretics each may be associated with increased serum potassium levels. The potential effects of indomethacin and potassium-sparing diuretics on potassium kinetics and renal function should be considered when these agents are administered concurrently.
  Most of the above effects concerning diuretics have been attributed, at least in part, to mechanisms involving inhibition of prostaglandin synthesis by indomethacin.
  During concomitant therapy with NSAIDs, the patient should be observed closely for signs of renal failure (see WARNINGS, Renal Effects), as well as to assure diuretic efficacy.
  Lithium
  Indomethacin capsules 50 mg t.i.d. produced a clinically relevant elevation of plasma lithium and reduction in renal lithium clearance in psychiatric patients and normal subjects with steady state plasma lithium concentrations. This effect has been attributed to inhibition of prostaglandin synthesis. As a consequence, when NSAIDs and lithium are given concomitantly, the patient should be carefully observed for signs of lithium toxicity. (Read circulars for lithium preparations before use of such concomitant therapy.) In addition, the frequency of monitoring serum lithium concentration should be increased at the outset of such combination drug treatment.
  Methotrexate
  NSAIDs have been reported to competitively inhibit methotrexate accumulation in rabbit kidney slices. This may indicate that they could enhance the toxicity of methotrexate. Caution should be used when NSAIDs are administered concomitantly with methotrexate.
  NSAIDs
  The concomitant use of indomethacin with other NSAIDs is not recommended due to the increased possibility of gastrointestinal toxicity, with little or no increase in efficacy.
  Oral anticoagulants
  Clinical studies have shown that indomethacin does not influence the hypoprothrombinemia produced by anticoagulants. However, when any additional drug, including indomethacin, is added to the treatment of patients on anticoagulant therapy, the patients should be observed for alterations of the prothrombin time. In post-marketing experience, bleeding has been reported in patients on concomitant treatment with anticoagulants and indomethacin. Caution should be exercised when indomethacin and anticoagulants are administered concomitantly. The effects of warfarin and NSAIDs on GI bleeding are synergistic, such that users of both drugs together have a risk of serious GI bleeding higher than users of either drug alone.
  Probenecid
  When indomethacin is given to patients receiving probenecid, the plasma levels of indomethacin are likely to be increased. Therefore, a lower total daily dosage of Indomethacin may produce a satisfactory therapeutic effect. When increases in the dose of Indomethacin are made, they should be made carefully and in small increments.
  DRUG/LABORATORY TEST INTERACTIONS
  False-negative results in the dexamethasone suppression test (DST) in patients being treated with indomethacin have been reported. Thus, results of the DST should be interpreted with caution in these patients.
  Carcinogenesis, Mutagenesis, Impairment of Fertility
  In an 81 week chronic oral toxicity study in the rat at doses up to 1 mg/kg/day, indomethacin had no tumorigenic effect.
  Indomethacin produced no neoplastic or hyperplastic changes related to treatment in carcinogenic studies in the rat (dosing period 73-110 weeks) and the mouse (dosing period 62-88 weeks) at doses up to 1.5 mg/kg/day.
  Indomethacin did not have any mutagenic effect in in vitro bacterial tests (Ames test and E. coli with or without metabolic activation) and a series of in vivo tests including the host-mediated assay, sex-linked recessive lethals in Drosophila, and the micronucleus test in mice.
  Indomethacin at dosage levels up to 0.5 mg/kg/day had no effect on fertility in mice in a two generation reproduction study or a two litter reproduction study in rats.
  Pregnancy
  Teratogenic Effects
  Pregnancy Category C
  Teratogenic studies were conducted in mice and rats at dosages of 0.5, 1.0, 2.0, and 4.0 mg/kg/day. Except for retarded fetal ossification at 4 mg/kg/day considered secondary to the decreased average fetal weights, no increase in fetal malformations was observed as compared with control groups. Other studies in mice reported in the literature using higher doses (5 to 15 mg/kg/day) have described maternal toxicity and death, increased fetal resorptions, and fetal malformations. Comparable studies in rodents using high doses of aspirin have shown similar maternal and fetal effects. However, animal reproduction studies are not always predictive of human response. There are no adequate and well-controlled studies in pregnant women.
  Indomethacin should be used during pregnancy only if the potential benefit justifies the potential risk to the fetus.
  Nonteratogenic Effects
  Because of the known effects of nonsteroidal anti-inflammatory drugs on the fetal cardiovascular system (closure of ductus arteriosus), use during pregnancy (particularly late pregnancy) should be avoided.
  The known effects of indomethacin and other drugs of this class on the human fetus during the third trimester of pregnancy include: constriction of the ductus arteriosus prenatally, tricuspid incompetence, and pulmonary hypertension; non-closure of the ductus arteriosus postnatally which may be resistant to medical management; myocardial degenerative changes, platelet dysfunction with resultant bleeding, intracranial bleeding, renal dysfunction or failure, renal injury/dysgenesis which may result in prolonged or permanent renal failure, oligohydramnios, gastrointestinal bleeding or perforation, and increased risk of necrotizing enterocolitis.
  In rats and mice, 4.0 mg/kg/day given during the last three days of gestation caused a decrease in maternal weight gain and some maternal and fetal deaths. An increased incidence of neuronal necrosis in the diencephalon in the live-born fetuses was observed. At 2.0 mg/kg/day, no increase in neuronal necrosis was observed as compared to the control groups. Administration of 0.5 or 4.0 mg/kg/day during the first three days of life did not cause an increase in neuronal necrosis at either dose level.
  Labor and Delivery
  In rat studies with NSAIDs, as with other drugs known to inhibit prostaglandin synthesis, an increased incidence of dystocia, delayed parturition, and decreased pup survival occurred. The effects of Indomethacin on labor and delivery in pregnant women are unknown.
  Use in Nursing Mothers
  Indomethacin is excreted in the milk of lactating mothers. Indomethacin is not recommended for use in nursing mothers.
  Pediatric Use
  Safety and effectiveness in pediatric patients 14 years of age and younger has not been established.
  Indomethacin should not be prescribed for pediatric patients 14 years of age and younger unless toxicity or lack of efficacy associated with other drugs warrants the risk.
  In experience with more than 900 pediatric patients reported in the literature or to the manufacturer who were treated with indomethacin capsules, side effects in pediatric patients were comparable to those reported in adults. Experience in pediatric patients has been confined to the use of indomethacin capsules.
  If a decision is made to use indomethacin for pediatric patients two years of age or older, such patients should be monitored closely and periodic assessment of liver function is recommended. There have been cases of hepatotoxicity reported in pediatric patients with juvenile rheumatoid arthritis, including fatalities. If indomethacin treatment is instituted, a suggested starting dose is 1 - 2 mg/kg/day given in divided doses. Maximum daily dosage should not exceed 3 mg/kg/day or 150 - 200 mg/day, whichever is less. Limited data are available to support the use of a maximum daily dosage of 4 mg/kg/day or 150 - 200 mg/day, whichever is less. As symptoms subside, the total daily dosage should be reduced to the lowest level required to control symptoms, or the drug should be discontinued.
  Geriatric Use
  As with any NSAID, caution should be exercised in treating the elderly (65 years and older) since advancing age appears to increase the possibility of adverse reactions (see WARNINGS, Gastrointestinal Effects - Risk of Ulceration, Bleeding, and Perforation and DOSAGE AND ADMINISTRATION). Elderly patients seem to tolerate ulceration or bleeding less well than other individuals and many spontaneous reports of fatal GI events are in this population (see WARNINGS, Gastrointestinal Effects - Risk of Ulceration, Bleeding, and Perforation).
  Indomethacin may cause confusion or, rarely, psychosis (see ADVERSE REACTIONS); physicians should remain alert to the possibility of such adverse effects in the elderly.
  This drug is known to be substantially excreted by the kidney and the risk of toxic reactions to this drug may be greater in patients with impaired renal function. Because elderly patients are more likely to have decreased renal function, care should be taken in dose selection and it may be useful to monitor renal function (see WARNINGS, Renal Effects).

ADVERSE REACTIONS SECTION

- The adverse reactions for indomethacin capsules listed in the following table have been arranged into two groups: (1) incidence greater than 1%; and (2) incidence less than 1%. The incidence for group (1) was obtained from 33 double-blind controlled clinical trials reported in the literature (1,092 patients). The incidence for group (2) was based on reports in clinical trials, in the literature, and on voluntary reports since marketing. The probability of a causal relationship exists between indomethacin and these adverse reactions, some of which have been reported only rarely.
  Incidence greater than 1% | Incidence less than 1%
  *Reactions occurring in 3% to 9% of patients treated with indomethacin. (Those reactions occurring in less than 3% of the patients are unmarked.)
  GASTROINTESTINAL
  nausea* with or without vomiting dyspepsia* (including indigestion, heartburn and epigastric pain) diarrhea abdominal distress or pain constipation | Anorexia bloating (includes distension) flatulence peptic ulcer gastroenteritis rectal bleeding proctitis single or multiple ulcerations, including perforation and hemorrhage of the esophagus, stomach, duodenum or small and large intestines intestinal ulceration associated with stenosis and obstruction | gastrointestinal bleeding without obvious ulcer formation and perforation of pre-existing sigmoid lesions (diverticulum, carcinoma, etc.) development of ulcerative colitis and regional ileitis ulcerative stomatitis toxic hepatitis and jaundice (some fatal cases have been reported) intestinal strictures (diaphragms)
  CENTRAL NERVOUS SYSTEM
  headache (11.7%) dizziness* vertigo somnolence depression and fatigue (including malaise and listlessness) | anxiety (includes nervousness) muscle weakness involuntary muscle movements insomnia muzziness psychic disturbances including psychotic episodes mental confusion drowsiness | light-headedness syncope paresthesia aggravation of epilepsy and parkinsonism depersonalization coma peripheral neuropathy convulsion dysarthria
  SPECIAL SENSES
  Tinnitus | ocular — corneal deposits and retinal disturbances, including those of the macula, have been reported in some patients on prolonged therapy with Indomethacin | blurred vision diplopia hearing disturbances, deafness
  CARDIOVASCULAR
  None | Hypertension hypotension tachycardia chest pain | congestive heart failure arrhythmia; palpitations
  METABOLIC
  none | Edema weight gain fluid retention flushing or sweating | Hyperglycemia glycosuria hyperkalemia
  INTEGUMENTARY
  None | Pruritus rash; urticaria petechiae or ecchymosis | exfoliative dermatitis erythema nodosum loss of hair Stevens-Johnson syndrome erythema multiforme toxic epidermal necrolysis
  HEMATOLOGIC
  None | Leucopenia bone marrow depression anemia secondary to obvious or occult gastrointestinal bleeding | aplastic anemia hemolytic anemia agranulocytosis thrombocytopenic purpura disseminated intravascular coagulation
  HYPERSENSITIVITY
  None | acute anaphylaxis acute respiratory distress rapid fall in blood pressure resembling a shock-like state angioedema | Dyspnea asthma purpura angiitis pulmonary edema fever
  GENITOURINARY
  None | Hematuria vaginal bleeding proteinuria nephrotic syndrome interstitial nephritis | BUN elevation renal insufficiency, including renal failure
  MISCELLANEOUS
  None | Epistaxis breast changes, including enlargement and tenderness, or gynecomastia
  *Reactions occurring in 3% to 9% of patients treated with indomethacin. (Those reactions occurring in less than 3% of the patients are unmarked.)
  Causal relationship unknown: Other reactions have been reported but occurred under circumstances where a causal relationship could not be established. However, in these rarely reported events, the possibility cannot be excluded. Therefore, these observations are being listed to serve as alerting information to physicians:
  Cardiovascular: Thrombophlebitis
  Hematologic: Although there have been several reports of leukemia, the supporting information is weak.
  Genitourinary: Urinary frequency.
  A rare occurrence of fulminant necrotizing fasciitis, particularly in association with Group Aβ hemolytic streptococcus, has been described in persons treated with non-steroidal anti-inflammatory agents, including indomethacin, sometimes with fatal outcome (see also PRECAUTIONS, General).

OVERDOSAGE SECTION

The following symptoms may be observed following overdosage: nausea, vomiting, intense headache, dizziness, mental confusion, disorientation, or lethargy. There have been reports of paresthesias, numbness, and convulsions.

Treatment is symptomatic and supportive. The stomach should be emptied as quickly as possible if the ingestion is recent. If vomiting has not occurred spontaneously, the patient should be induced to vomit with syrup of ipecac. If the patient is unable to vomit, gastric lavage should be performed. Once the stomach has been emptied, 25 or 50 g of activated charcoal may be given. Depending on the condition of the patient, close medical observation and nursing care may be required. The patient should be followed for several days because gastrointestinal ulceration and hemorrhage have been reported as adverse reactions of indomethacin. Use of antacids may be helpful.

The oral LD50 of indomethacin in mice and rats (based on 14 day mortality response) was 50 and 12 mg/kg, respectively.

DOSAGE & ADMINISTRATION SECTION

- Carefully consider the potential benefits and risks of indomethacin and other treatment options before deciding to use indomethacin. Use the lowest effective dose for the shortest duration consistent with individual patient treatment goals (see WARNINGS).
  After observing the response to initial therapy with indomethacin, the dose and frequency should be adjusted to suit an individual patient’s needs.
  Indomethacin is available as 25 and 50 mg capsules.
  Adverse reactions appear to correlate with the size of the dose of indomethacin in most patients but not all. Therefore, every effort should be made to determine the smallest effective dosage for the individual patient.
  Pediatric Use
  Indomethacin ordinarily should not be prescribed for pediatric patients 14 years of age and under (see PRECAUTIONS, Pediatric Use).
  Adult Use
  Dosage Recommendations for Active Stages of the Following:
  1. Moderate to severe rheumatoid arthritis including acute flares of chronic disease; moderate to severe ankylosing spondylitis; and moderate to severe osteoarthritis.
    Suggested Dosage:
    Indomethacin capsules 25 mg b.i.d. or t.i.d. If this is well tolerated, increase the daily dosage by 25 or by 50 mg, if required by continuing symptoms, at weekly intervals until a satisfactory response is obtained or until a total daily dose of 150 - 200 mg is reached. DOSES ABOVE THIS AMOUNT GENERALLY DO NOT INCREASE THE EFFECTIVENESS OF THE DRUG.
    In patients who have persistent night pain and/or morning stiffness, the giving of a large portion, up to a maximum of 100 mg, of the total daily dose at bedtime, either orally or by rectal suppositories, may be helpful in affording relief. The total daily dose should not exceed 200 mg. In acute flares of chronic rheumatoid arthritis, it may be necessary to increase the dosage by 25 mg or, if required, by 50 mg daily.
    If minor adverse effects develop as the dosage is increased, reduce the dosage rapidly to a tolerated dose and OBSERVE THE PATIENT CLOSELY.
    If severe adverse reactions occur, STOP THE DRUG. After the acute phase of the disease is under control, an attempt to reduce the daily dose should be made repeatedly until the patient is receiving the smallest effective dose or the drug is discontinued.
    Careful instructions to, and observations of, the individual patient are essential to the prevention of serious, irreversible, including fatal, adverse reactions.
    As advancing years appear to increase the possibility of adverse reactions, indomethacin should be used with greater care in the elderly (see PRECAUTIONS, Geriatric Use).
  2. Acute painful shoulder (bursitis and/or tendinitis).
    Initial Dose:
    75 mg to 150 mg daily in 3 or 4 divided doses.
    The drug should be discontinued after the signs and symptoms of inflammation have been controlled for several days. The usual course of therapy is 7 to 14 days.
  3. Acute gouty arthritis.
    Suggested Dose:
    Indomethacin capsules 50 mg t.i.d. until pain is tolerable. The dose should then be rapidly reduced to complete cessation of the drug. Definite relief of pain has been reported within 2 to 4 hours. Tenderness and heat usually subside in 24 to 36 hours, and swelling gradually disappears in 3 to 5 days.